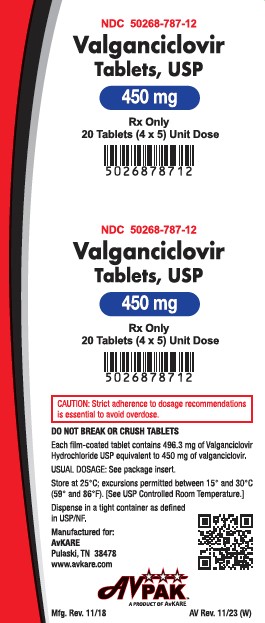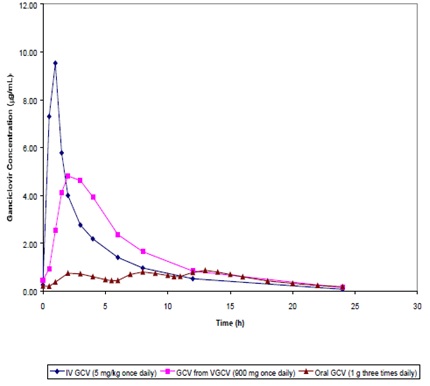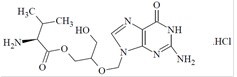 DRUG LABEL: Valganciclovir
NDC: 50268-787 | Form: TABLET, FILM COATED
Manufacturer: AvPAK
Category: prescription | Type: HUMAN PRESCRIPTION DRUG LABEL
Date: 20251231

ACTIVE INGREDIENTS: VALGANCICLOVIR HYDROCHLORIDE 450 mg/1 1
INACTIVE INGREDIENTS: POLYETHYLENE GLYCOL, UNSPECIFIED; CROSPOVIDONE; CELLULOSE, MICROCRYSTALLINE; POVIDONE; STEARIC ACID; HYPROMELLOSES; FERRIC OXIDE RED; POLYSORBATE 80; TITANIUM DIOXIDE

HIGHLIGHTS OF PRESCRIBING INFORMATION

Valganciclovir Tablet, USP
HIGHLIGHTS OF PRESCRIBING INFORMATION
These highlights do not include all the information needed to use VALGANCICLOVIR TABLETS safely and effectively. See full prescribing information for VALGANCICLOVIR TABLETS.
VALGANCICLOVIR Tablets USP, for oral use
Initial U.S. Approval: 2001

RECENT MAJOR CHANGES

Indications and Usage, Pediatric Patients (1.2) 04/2015
Dosage and Administration, Pediatric Patients (2.3) 04/2015

BOXED WARNING

WARNING: HEMATOLOGIC TOXICITY, IMPAIRMENT OF FERTILITY, FETAL TOXICITY, MUTAGENESIS AND CARCINOGENESIS
See full prescribing information for complete boxed warning.
• Hematologic Toxicity: Severe leukopenia, neutropenia, anemia thrombocytopenia, pancytopenia, bone marrow aplasia and aplastic anemia have been reported in patients treated with
valganciclovir tablets (5.1).
• Impairment of Fertility: Based on animal data, valganciclovir tablets may cause temporary or permanent inhibition of spermatogenesis (5.2).
• Fetal Toxicity: Based on animal data, valganciclovir tablets have the potential to cause birth defects in humans (5.3).
• Mutagenesis and Carcinogenesis: Based on animal data, valganciclovir tablets have the potential to cause cancers in humans (5.4).

1 INDICATIONS & USAGE

Valganciclovir tablets, USP are a cytomegalovirus (CMV) nucleoside analogue DNA polymerase inhibitor indicated for:
Adult Patients (1.1)
• Treatment of CMV retinitis in patients with acquired immunodeficiency syndrome (AIDS).
• Prevention of CMV disease in kidney, heart, and kidney-pancreas transplant patients at high risk.
Pediatric Patients (1.2)
• Prevention of CMV disease in heart transplant patients at high risk.

2 DOSAGE & ADMINISTRATION

Adult Dosage (2.2)
Treatment of CMV retinitis | Induction: 900 mg (two 450 mg tablets) twice a day for 21 days Maintenance: 900 mg (two 450 mg tablets) once a day
Prevention of CMV disease in heart or kidney-pancreas transplant patients | 900 mg (two 450 mg tablets) once a day within 10 days of transplantation until 100 days post-transplantation
Prevention of CMV disease in kidney transplant patients | 900 mg (two 450 mg tablets) once a day within 10 days of transplantation until 200 days post-transplantation
Pediatric Dosage (2.3)
Prevention of CMV disease in heart transplant patients 4 months to 16 years of age | Dose once a day within 10 days of transplantation until 100 days post-transplantation according to dosage algorithm (note the calculation of creatinine clearance using a modified Schwartz formula in children)

• Valganciclovir tablets should be taken with food (2.1, 12.3).
• Valganciclovir tablets should not be broken or crushed (2.6).
• Adult patients should use valganciclovir tablets, not valganciclovir for oral solution (2.1).
• Adults with renal impairment: Adjust dose based on creatinine clearance. For adult patients receiving hemodialysis a dose recommendation cannot be given (2.5, 8.6,12.3).

3 DOSAGE FORMS & STRENGTHS

• Tablets: 450 mg (3)

4 CONTRAINDICATIONS

Hypersensitivity to valganciclovir or ganciclovir (4)

5 WARNINGS AND PRECAUTIONS

• Hematologic toxicity: Severe leukopenia, neutropenia, anemia, thrombocytopenia, pancytopenia, bone marrow depression, and aplastic anemia have occurred with the use of valganciclovir tablets
or ganciclovir. Avoid valganciclovir tablets use if absolute neutrophil count is less than 500 cells/µL, platelet count is less than 25,000/µL, or hemoglobin is less than 8 g/dL. Use with caution in
pre-existing cytopenias and when receiving myelosuppressive drugs or irradiation. Monitor with frequent testing of platelet and complete blood counts (5.1).
• Impairment of fertility: Based on animal studies, valganciclovir tablets may cause temporary or permanent inhibition of spermatogenesis (5.2).
• Fetal toxicity: Based on animal studies, valganciclovir tablets may cause fetal harm. Females of reproductive potential should use effective contraception during and following treatment and males
should practice barrier contraception during and following treatment (5.3).
• Mutagenicity and carcinogenicity: Based on animal studies, valganciclovir tablets are potentially mutagenic and carcinogenic (5.4).
• Acute renal failure: Acute renal failure may occur in elderly patients (with or without reduced renal function), patients who receive concomitant nephrotoxic drugs, or inadequately hydrated patients. Use
with caution in elderly patients or those taking nephrotoxic drugs, reduce dosage in patients with renal impairment, and monitor renal function (2.5, 5.5, 8.5, 8.6, 12.3).

6 ADVERSE REACTIONS

• Adult patients: Most common adverse events and laboratory abnormalities (reported in at least one indication by greater than or equal to 20% of patients) are diarrhea, pyrexia, nausea, tremor,
neutropenia, anemia, graft rejection, thrombocytopenia, and vomiting (6.1).
• Pediatric patients: Most common adverse events and laboratory abnormalities (reported in greater than or equal to 20% of pediatric solid organ transplant recipients) are diarrhea, pyrexia,
hypertension, upper respiratory tract infection, urinary tract infection, vomiting, neutropenia, leukopenia, and headache (6.1).
To report SUSPECTED ADVERSE REACTIONS, contact AvKARE, Inc. at 1-855-361-3993 or FDA at 1-800-FDA-1088 or www.fda.gov/medwatch.

7 DRUG INTERACTIONS

• Zidovudine: Potential to cause neutropenia and anemia. Monitor with frequent tests of white blood cell counts with differential and hemoglobin levels (7).
• Probenecid: May increase ganciclovir levels. Monitor for evidence of ganciclovir toxicity (7).
• Mycophenolate mofetil (MMF): May increase ganciclovir concentrations and levels of MMF metabolites in patients with renal impairment. Monitor for ganciclovir and MMF toxicity (7).
• Didanosine: May increase didanosine concentrations. Monitor for didanosine toxicity (7).

8 USE IN SPECIFIC POPULATIONS

• Lactation: Breastfeeding is not recommended with use of valganciclovir tablets (8.2)
See 17 for PATIENT COUNSELING INFORMATION and FDA-approved patient labeling

Pediatric use information for pediatric kidney transplant patients ages 4 months to 16 years and for pediatric heart transplant patients ages 1 to less than 4 months is approved for Roche Palo Alto
LLC' s VALCYTE (valganciclovir hydrochloride) tablets. However, due to Roche Palo Alto LLC' s marketing exclusivity rights, this drug product is not labeled with that pediatric information.

FULL PRESCRIBING INFORMATION

BOXED WARNING

WARNING: HEMATOLOGIC TOXICITY, IMPAIRMENT OF FERTILITY, FETAL TOXICITY, MUTAGENESIS AND CARCINOGENESIS

• Hematologic Toxicity: Severe leukopenia, neutropenia, anemia, thrombocytopenia, pancytopenia, bone marrow aplasia and aplastic anemia have been reported in patients treated with valganciclovir
tablets [see Warnings and Precautions (5.1)].
• Impairment of Fertility: Based on animal data, valganciclovir tablets may cause temporary or permanent inhibition of spermatogenesis [see Warnings and Precautions (5.2)].
• Fetal Toxicity: Based on animal data, valganciclovir tablets have the potential to cause birth defects in humans [see Warnings and Precautions (5.3)].
• Mutagenesis and Carcinogenesis: Based on animal data, valganciclovir tablets have the potential to cause cancers in humans [see Warnings and Precautions (5.4)].

1 INDICATIONS & USAGE

1.1 Adult Patients

Treatment of Cytomegalovirus (CMV) Retinitis: Valganciclovir tablets, USP are indicated for the treatment of CMV retinitis in patients with acquired immunodeficiency syndrome (AIDS) [see Clinical Studies (14.1)].
Prevention of CMV Disease: Valganciclovir tablets, USP are indicated for the prevention of CMV disease in kidney, heart, and kidney-pancreas transplant patients at high risk (Donor CMV seropositive/Recipient CMV seronegative [D+/R-]) [see Clinical Studies (14.1)].

1.2 Pediatric Patients

Prevention of CMV Disease: Valganciclovir tablets, USP are indicated for the prevention of CMV disease in heart transplant patients (4 month to 16 years of age) at high risk [see Clinical Studies (14.2)].
Pediatric use information for pediatric kidney transplant patients ages 4 months to 16 years and for pediatric heart transplant patients ages 1 to less than 4 months is approved for Roche
Palo Alto LLC' s VALCYTE (valganciclovir hydrochloride) tablets. However, due to Roche Palo Alto LLC' s marketing exclusivity rights, this drug product is not labeled with that pediatric information.

2 DOSAGE & ADMINISTRATION

2.1 General Dosing Information

• Adult patients should use valganciclovir tablets, not valganciclovir for oral solution.
• Valganciclovir tablets should be taken with food [see Clinical Pharmacology (12.3)].

2.2 Recommended Dosage in Adult Patients with Normal Renal Function

For dosage recommendations in adult patients with renal impairment [see Dosage and Administration (2.5)].
Treatment of CMV Retinitis:
• Induction: The recommended dosage is 900 mg (two 450 mg tablets) taken orally twice a day for 21 days.
• Maintenance: Following induction treatment, or in adult patients with inactive CMV retinitis, the recommended dosage is 900 mg (two 450 mg tablets) taken orally once a day.
Prevention of CMV Disease:
• For adult patients who have received a heart or kidney-pancreas transplant, the recommended dosage is 900 mg (two 450 mg tablets) taken orally once a day starting within 10 days
of transplantation until 100 days post-transplantation.
• For adult patients who have received a kidney transplant, the recommended dosage is 900 mg (two 450 mg tablets) taken orally once a day starting within 10 days of transplantation until 200
days post-transplantation.

2.3 Recommended Dosage in Pediatric Patients

Prevention of CMV Disease in Pediatric Heart Transplant Patients: For pediatric heart transplant patients 4 month to 16 years of age, the recommended once daily mg dose (7x BSA x CrCL) should start within 10 days of transplantation until 100 days post-transplantation.
The recommended once daily dosage of valganciclovir is based on body surface area (BSA) and creatinine clearance (CrCl) derived from a modified Schwartz formula, and is calculated using the equation below:
Pediatric Dose (mg) = 7 x BSA x CrCl (calculated using a modified Schwartz formula). If the calculated Schwartz creatinine clearance exceeds 150 mL/min/1.73m^2, then a maximum value of 150 mL/min/1.73m^2 should be used in the equation. The k values used in the modified Schwartz formula are based on pediatric patient age, as shown in Table 1.
Mosteller BSA (m^2) = √ Height (cm) x weight (kg)
3600
Schwartz Creatinine Clearance (mL/min/1.73m^2) = K x Height (cm)
Serum Creatinine (mg/dL)
Table 1. k Values According to Pediatric Patient Age*

k value | Pediatric Patient Age
0.33 | Infants less than 1 year of age with low birth weight for gestational age
0.45 | Infants less than 1 year of age with birth weight appropriate for gestational age
0.45 | Children aged 1 to less than 2 years
0.55 | Boys aged 2 to less than 13 years Girls aged 2 to less than 16 years
0.7 | Boys aged 13 to 16 years

* The k values provided are based on the Jaffe method of measuring serum creatinine, and may require correction when enzymatic methods are used^1
Monitor serum creatinine levels regularly and consider changes in height and body weight and adapt the dose as appropriate during prophylaxis period.
All calculated doses should be rounded to the nearest 10 mg increment for the actual deliverable dose. If the calculated dose exceeds 900 mg, a maximum dose of 900 mg should be administered. Valganciclovir for oral solution is the preferred formulation since it provides the ability to administer a dose calculated according to the formula above; however, valganciclovir tablets may be used if the calculated doses are within 10% of available tablet strength (450 mg). For example, if the calculated dose is between 405 mg and 495 mg, one 450 mg tablet may be taken. Before prescribing valganciclovir tablets, pediatric patients should be assessed for the ability to swallow tablets. Pediatric use information for pediatric kidney transplant patients ages 4 months to 16 years and for pediatric heart transplant patients ages 1 to less than 4 months is approved for Roche Palo Alto LLC' s VALCYTE (valganciclovir hydrochloride) tablets. However, due to Roche Palo Alto LLC' s marketing exclusivity rights, this drug product is not labeled with that pediatric information.

2.5 Dosage Recommendation for Adult Patients with Renal Impairment

Serum creatinine levels or creatinine clearance should be monitored regularly during treatment. Dosage recommendations for adult patients with reduced renal function are provided in Table 2.
For adult patients on hemodialysis (CrCl less than 10 mL/min), a dose recommendation for valganciclovir tablets cannot be given [see Use in Specific Populations (8.5,8.6), Clinical Pharmacology (12.3)].
Table 2 Dosage Recommendations for Adult Patients with Impaired Renal Function

Valganciclovir Tablets 450 mg
CrCl* (mL/min) | Induction Dose | Maintenance/Prevention Dose
≥ 60 | 900 mg twice daily | 900 mg once daily
40 – 59 | 450 mg twice daily | 450 mg once daily
25 – 39 | 450 mg once daily | 450 mg every 2 days
10 – 24 | 450 mg every 2 days | 450 mg twice weekly
< 10 (on hemodialysis) | not recommended | not recommended

*An estimated creatinine clearance in adults is calculated from serum creatinine by the following formulas:
For males = (140-age [years]) x (body weight [kg])
(72) x (serum creatinine [mg/dL]
For females = 0.85 x male value
Dosing in pediatric patients with renal impairment can be done using the recommended equations because CrCl is a component in the calculation [see Dosage and Administration (2.3)].

2.6 Handling and Disposal

Caution should be exercised in the handling of valganciclovir tablets. Tablets should not be broken or crushed. Because valganciclovir is considered a potential teratogen and carcinogen in humans, caution should be observed in handling broken tablets [see Warnings and Precautions (5.3,5.4)]. Avoid direct contact with broken or crushed tablets with skin or mucous membranes. If such contact occurs, wash thoroughly with soap and water, and rinse eyes thoroughly with plain water.
Handle and dispose valganciclovir tablets according to guidelines for antineoplastic drugs because ganciclovir shares some of the properties of antitumor agents (i.e., carcinogenicity and mutagenicity)2.

3 DOSAGE FORMS & STRENGTHS

450 mg, pink, oval, biconvex, film-coated tablets, debossed with "J" on one side and "156" on the other side.

4 CONTRAINDICATIONS

Valganciclovir tablets are contraindicated in patients who have had a demonstrated clinically significant hypersensitivity reaction (e.g., anaphylaxis) to valganciclovir, ganciclovir, or any component of the formulation [see Adverse Reactions (6.1)].

5 WARNINGS AND PRECAUTIONS

5.1Hematologic Toxicity

Severe leukopenia, neutropenia, anemia, thrombocytopenia, pancytopenia, bone marrow aplasia, and aplastic anemia have been reported in patients treated with valganciclovir tablets or ganciclovir. Valganciclovir tablets should be avoided if the absolute neutrophil count is less than 500 cells/µL, the platelet count is less than 25,000/µL, or the hemoglobin is less than 8 g/dL. Valganciclovir tablets should also be used with caution in patients with pre-existing cytopenias, or who have received or who are receiving myelosuppressive drugs or irradiation. Cytopenia may occur at any time during treatment and may worsen with continued dosing. Cell counts usually begin to recover within 3 to 7 days after discontinuing drug.
Due to the frequency of neutropenia, anemia, and thrombocytopenia in patients receiving valganciclovir tablets [see Adverse Reactions (6.1)], complete blood counts with differential and platelet counts should be performed frequently, especially in patients in whom ganciclovir or other nucleoside analogues have previously resulted in leukopenia, or in whom neutrophil counts are less than 1000 cells/μL at the beginning of treatment. Increased monitoring for cytopenias may be warranted if therapy with oral ganciclovir is changed to valganciclovir tablets, because of increased plasma concentrations of ganciclovir after valganciclovir tablets administration [see Clinical Pharmacology (12.3)].

5.2 Impairment of Fertility

Based on animal data with ganciclovir, valganciclovir tablets at the recommended human doses may cause temporary or permanent inhibition of spermatogenesis in males, and may cause suppression of fertility in females. Advise patients that fertility may be impaired with use of valganciclovir tablets [see Use in Specific Populations (8.1,8.3), Nonclinical Toxicology (13.1)].

5.3 Fetal Toxicity

Ganciclovir may cause fetal toxicity when administered to pregnant women based on findings in animal studies. When given to pregnant rabbits at dosages resulting in 2-times the human exposure (based on AUC), ganciclovir caused malformations in multiple organs of the fetuses. Maternal and fetal toxicity were also observed in pregnant mice and rabbits. Therefore, valganciclovir has the potential to cause birth defects. Pregnancy should be avoided in female patients taking valganciclovir tablets and in females with male partners taking valganciclovir tablets. Females of reproductive potential should be advised to use effective contraception during treatment and for at least 30 days following treatment with valganciclovir tablets. Similarly, males should be advised to practice barrier contraception during and for at least 90 days following treatment with valganciclovir tablets [see Dosage and Administration (2.6), Use in Specific Populations (8.1,8.3), Nonclinical Toxicology (13.1)].

5.4 Mutagenesis and Carcinogenesis

Animal data indicate that ganciclovir is mutagenic and carcinogenic. Valganciclovir tablets should therefore be considered a potential carcinogen in humans [see Dosage and Administration (2.6), Nonclinical Toxicology (13.1)].

5.5 Acute Renal Failure

Acute renal failure may occur in:
• Elderly patients with or without reduced renal function. Caution should be exercised when administering valganciclovir tablets to geriatric patients, and dosage reduction is recommended for
those with impaired renal function [see Dosage and Administration (2.5), Use in Specific Populations (8.5, 8.6)].
• Patients receiving potential nephrotoxic drugs. Caution should be exercised when administering valganciclovir tablets to patients receiving potential nephrotoxic drugs.
• Patients without adequate hydration. Adequate hydration should be maintained for all patients.

6 ADVERSE REACTIONS

The following serious adverse events are discussed in greater detail in other sections of the labeling:
• Hematologic toxicity [see Boxed Warning, Warnings and Precautions (5.1)].
• Acute renal failure [see Warnings and Precautions (5.5)].
The most common adverse events and laboratory abnormalities reported in at least one indication by greater than or equal to 20% of adult patients treated with valganciclovir tablets are diarrhea, pyrexia, nausea, tremor, neutropenia, anemia, graft rejection, thrombocytopenia, and vomiting. The most common reported adverse events and laboratory abnormalities reported in greater than or equal to 20% of pediatric solid organ transplant recipients treated with valganciclovir tablets are diarrhea, pyrexia, hypertension, upper respiratory tract infection, urinary tract infection, vomiting, neutropenia, leukopenia, and head ache.

6.1 Clinical Trials Experience

Because clinical trials are conducted under widely varying conditions, adverse event rates observed in the clinical trials of a drug cannot be directly compared to rates in the clinical trials of another drug and may not reflect rates observed in practice.
Valganciclovir, a prodrug of ganciclovir, is rapidly converted to ganciclovir after oral administration. Adverse events known to be associated with ganciclovir usage can therefore be expected to occur with valganciclovir tablets.
Adverse Events in Adults:
Treatment of CMV Retinitis in AIDS Patients: In a clinical study for the treatment of CMV retinitis in HIV-infected patients, the adverse events reported by patients receiving valganciclovir tablets (n=79) or intravenous ganciclovir (n=79) for 28 days of randomized therapy (21 days induction dose and 7 days maintenance dose), respectively, included diarrhea (16%, 10%), nausea (8%, 14%), headache (9%, 5%), and catheter-related infections (3%, 11%). The incidence of adverse events was similar between the group who received valganciclovir tablets and the group who received intravenous ganciclovir, with the exception of catheter-related infections, which occurred with greater frequency in patients randomized to receive intravenous ganciclovir. The frequencies of neutropenia (ANC less than 500/μL) were 11% for patients receiving valganciclovir tablets compared with 13% for patients receiving intravenous ganciclovir. Anemia (Hgb less than 8 g/dL) occurred in 8% of patients in each group. Other laboratory abnormalities occurred with similar frequencies in the two groups.
Adverse events and abnormal laboratory values data are available for 370 patients who received maintenance therapy with valganciclovir tablets 900 mg once daily in two open-label clinical trials. Approximately 252 (68%) of these patients received valganciclovir tablets for more than nine months (maximum duration was 36 months). Table 3 and Table 4 show the pooled adverse event data and abnormal laboratory values from these patients.
Table 3 Pooled Selected Adverse Events Reported in greater than or equal to 5% of Patients who Received Valganciclovir Tablets Maintenance Therapy for CMV Retinitis

 | Patients with CMV Retinitis
Adverse Events According to Body System | Valganciclovir Tablets (N=370) %
Gastrointestinal system
Diarrhea | 41
Nausea | 30
Vomiting | 21
Abdominal pain | 15
Body as a Whole
Pyrexia | 31
Headache | 22
Central and peripheral nervous system
Insomnia | 16
Peripheral neuropathy | 9
Paresthesia | 8
Special senses
Retinal detachment | 15

Table 4 Pooled Laboratory Abnormalities Reported in Patients Who Received Valganciclovir Tablets Maintenance Therapy for the Treatment of CMV Retinitis

 | Patients with CMV Retinitis
Laboratory Abnormalities | Valganciclovir Tablets (N=370) %
Neutropenia: ANC/µL
< 500 | 19
500 – < 750 | 17
750 – <1000 | 17
Anemia: Hemoglobin g/dL
< 6.5 | 7
6.5 – < 8 | 13
8 – <9.5 | 16
Thrombocytopenia: Platelets/µL
<25000 | 4
25000 – < 50000 | 6
50000 – < 100000 | 22
Serum Creatinine: mg/dL
> 2.5 | 3
> 1.5 – 2.5 | 12

Prevention of CMV Disease in Selected Solid Organ Transplantation: Table 5 shows selected adverse events regardless of severity and drug relationship with an incidence of greater than or equal to 5% from a clinical trial (up to 28 days after study treatment) where heart, kidney, kidney-pancreas and liver transplant patients received valganciclovir tablets (N=244) or oral ganciclovir (N=126) until Day 100 post-transplant. The majority of the adverse events were of mild or moderate intensity.
Table 5 Percentage of Selected Grades 1 to 4 Adverse Events Reported in greater than or equal to 5% of Adult Patients from a Study of Solid Organ Transplant Patients

Adverse Event | Valganciclovir Tablets (N=244) % | Oral Ganciclovir (N=126) %
Diarrhea | 30 | 29
Tremors | 28 | 25
Graft rejection | 24 | 30
Nausea | 23 | 23
Headache | 22 | 27
Insomnia | 20 | 16
Hypertension | 18 | 15
Vomiting | 16 | 14
Pyrexia | 13 | 14

Table 6 shows selected adverse events regardless of severity and drug relationship with an incidence of greater than or equal to 5% from another clinical trial where kidney transplant patients received either valganciclovir once daily starting within 10 days post-transplant until Day 100 post-transplant followed by 100 days of placebo or valganciclovir once daily starting within 10 days post-transplant until Day 200 post-transplant. The overall safety profile of valganciclovir tablets did not change with the extension of prophylaxis until Day 200 post-transplant in high risk kidney transplant patients.
Table 6 Percentage of Selected Grades 1 to 4 Adverse Events Reported in greater than or equal to 5% of Adult Patients from a Study of Kidney Transplant Patients

Adverse Event | Valganciclovir Tablets Day 100 Post-transplant (N=164) % | Valganciclovir Tablets Day 200 Post-transplant (N=156) %
Diarrhea | 26 | 31
Tremors | 12 | 17
Hypertension | 13 | 12
Nausea | 11 | 11
Pyrexia | 12 | 9
Transplant rejection | 9 | 6
Headache | 10 | 6
Insomnia | 7 | 6
Vomiting | 3 | 6

Adverse events not included in Table 5 and Table 6, which either occurred at a frequency of greater than or equal to 5% in clinical studies with solid organ transplant patients, or were selected serious adverse events reported in studies with patients with CMV retinitis or in studies with solid organ transplant patients with a frequency of less than 5% are listed below.
Allergic reactions: valganciclovir hypersensitivity
Bleeding complications: potentially life-threatening bleeding associated with thrombocytopenia
Central and peripheral nervous system: paresthesia, dizziness (excluding vertigo), convulsion
Gastrointestinal disorders: abdominal pain, constipation, dyspepsia, abdominal distention, ascites
General disorders and administration site disorders: fatigue, pain, edema, peripheral edema, weakness
Hemic system: anemia, neutropenia, thrombocytopenia, pancytopenia, bone marrow depression, aplastic anemia, febrile neutropenia
Hepatobiliary disorders: abnormal hepatic function
Infections and infestations: pharyngitis/nasopharyngitis, upper respiratory tract infection, urinary tract infection, local and systemic infections and sepsis, postoperative wound infection
Injury, poisoning, and procedural complications: postoperative complications, postoperative pain, increased wound drainage, wound dehiscence
Metabolism and nutrition disorders: hyperkalemia, hypokalemia, hypomagnesemia, hyperglycemia, appetite decreased, dehydration, hypophosphatemia, hypocalcemia
Musculoskeletal and connective tissue disorders: back pain, arthralgia, muscle cramps, limb pain
Psychiatric disorders: depression, psychosis, hallucinations, confusion, agitation
Renal and urinary disorders: renal impairment, dysuria, decreased creatinine clearance
Respiratory, thoracic and mediastinal disorders: cough, dyspnea, rhinorrhea, pleural effusion
Skin and subcutaneous tissue disorders: dermatitis, pruritus, acne
Vascular disorders: hypotension
Laboratory abnormalities reported with valganciclovir tablets in two studies in adult solid organ transplant patients are listed in Table 7 and Table 8.
Table 7 Selected Laboratory Abnormalities Reported in a Study of Adult Solid Organ Transplant Patients*

Laboratory Abnormalities | Valganciclovir Tablets (N=244) % | Ganciclovir Capsules (N=126) %
Neutropenia: ANC/µL< 500 500 – < 750 750 – < 1000 | 5 3 5 | 3 2 2
Anemia: Hemoglobin g/dL< 6.5 6.5 – < 8 8 – <9.5 | 1 5 31 | 2 7 25
Thrombocytopenia: Platelets/µL<25000 25000 – < 50000 50000 – < 100000 | 0 1 18 | 2 3 21
Serum Creatinine: mg/dL > 2.5 > 1.5 – 2.5 | 14 45 | 21 47

*Laboratory abnormalities are those reported by investigators.

Table 8 Selected Laboratory Abnormalities Reported in a Study of Adult Kidney Transplant Patients*

Laboratory Abnormalities | Valganciclovir Tablets Day 100 Post-transplant (N=164) % | Valganciclovir Tablets Day 200 Post-transplant (N=156) %
Neutropenia: ANC/µL< 500 500 – < 750 750 – <1000 | 9 6 7 | 10 6 5
Anemia: Hemoglobin g/dL< 6.5 6.5 – < 8 8 – <9.5 | 05 17 | 1 1 15
Thrombocytopenia: Platelets/µL<25000 25000 – < 50000 50000 – < 100000 | 0 1 7 | 00 3
Serum Creatinine: mg/dL> 2.5 > 1.5 – 2.5 | 17 50 | 14 48

*Laboratory abnormalities are those reported by investigators.

Adverse Events in Pediatric Patients:
Valganciclovir tablets have been studied in 109 pediatric solid organ transplant patients who were at risk for developing CMV disease (aged 4 months to 16 years) and in 24 neonates with symptomatic congenital CMV disease (aged 8 to 34 days), with duration of ganciclovir exposure ranging from 2 to 100 days [see Use in Specific Populations (8.4), Clinical Studies (14.2)].
Prevention of CMV Disease in Pediatric Solid Organ Transplant Patients: The most frequently reported adverse events (greater than 10% of patients), regardless of seriousness and drug relationship in pediatric solid organ transplant patients taking valganciclovir tablets until Day 100 post-transplant were diarrhea, pyrexia, upper respiratory tract infection, hypertension, vomiting, anemia, neutropenia, constipation, nausea and transplant rejection.
In general, the safety profile was similar in pediatric patients compared to that observed in adult patients. However, the rates of certain adverse events and laboratory abnormalities, such as upper respiratory tract infection, pyrexia, nasopharyngitis, anemia, and abdominal pain were reported more frequently in pediatric patients than in adults [see Use in Specific Populations (8.4), Clinical Studies (14.2)]. Neutropenia was reported with higher incidence in the two pediatric studies as compared to adults, but there was no correlation between neutropenia and infections observed in the pediatric population.
Pediatric use information for pediatric kidney transplant patients ages 4 months to 16 years and for pediatric heart transplant patients ages 1 to less than 4 months is approved for Roche Palo Alto LLC' s VALCYTE (valganciclovir hydrochloride) tablets. However, due to Roche Palo Alto LLC' s marketing exclusivity rights, this drug product is not labeled with that pediatric information.

6.2 Postmarketing Experience

The following adverse events have been identified during post-approval use of valganciclovir tablets. Because these reactions are reported voluntarily from a population of uncertain size, it is not always possible to reliably estimate their frequency or establish a causal relationship to drug exposure. As valganciclovir tablets are rapidly and extensively converted to ganciclovir, any adverse events associated with ganciclovir might also occur with valganciclovir.– Anaphylaxis
– Decreased fertility in males
In general, the adverse events reported during the postmarketing use of valganciclovir tablets were similar to those identified during the clinical trials.

In general, the adverse events reported during the postmarketing use of valganciclovir tablets were similar to those identied during the clinical trials.

To report SUSPECTED ADVERSE REACTIONS, contact AvKARE at 1-855-361-3993 or FDA at 1-800-FDA-1088 or www.fda.gov/medwatch.

7 DRUG INTERACTIONS

In vivo drug-drug interaction studies were not conducted with valganciclovir. However, because valganciclovir is rapidly and extensively converted to ganciclovir, drug-drug interactions associated with ganciclovir will be expected for valganciclovir tablets. Established and other potentially significant drug interactions conducted with ganciclovir are listed in Table 9.
Table 9 Established and Other Potentially Significant Drug Interactions with Ganciclovir

Name of the Concomitant Drug | Change in the Concentration of Ganciclovir or Concomitant Drug | Clinical Comment
Zidovudine | ↓ Ganciclovir ↑ Zidovudine | Zidovudine and valganciclovir tablets each have the potential to cause neutropenia and anemia
Probenicid | ↑ Ganciclovir | Patients taking probenicid and valganciclovir tablets should be monitored for evidence of ganciclovir toxicity
Mycophenolate Mofetil (MMF) | ↔ Ganciclovir (in patients with normal renal function) ↔ MMF (in patients with normal renal function) | Patients with renal impairment should be monitored carefully as levels of MMF metabolites and ganciclovir may increase
Didanosine | ↓ Ganciclovir ↑ Didanosine | Patients should be closely monitored for didanosine toxicity

8 USE IN SPECIFIC POPULATIONS

8.1 Pregnancy

Teratogenic Effects
Risk Summary
After oral administration, valganciclovir (prodrug) is converted to ganciclovir (active drug) and, therefore, valganciclovir tablets are expected to have reproductive toxicity effects similar to ganciclovir. In animal studies, ganciclovir caused maternal and fetal toxicity and embryo-fetal mortality in pregnant mice and rabbits as well as teratogenicity in rabbits at exposures two-times the human exposure. There are no available human data on use of valganciclovir tablets or ganciclovir in pregnant women to establish the presence or absence of drug-associated risk. The background risk of major birth defects and miscarriage for the indicated populations is unknown. However, the background risk in the U.S. general population of major birth defects is 2 to 4% and the risk of miscarriage is 15 to 20% of clinically recognized pregnancies. Advice pregnant women of the potential risk to the fetus [see Warnings and Precautions (5.3), Use in Specific Populations (8.3)].
Clinical Considerations
Disease-associated maternal and/or embryo/fetal risk
Most maternal CMV infections are asymptomatic or they may be associated with a self-limited mononucleosis-like syndrome. However, in immunocompromised patients (i.e., transplant patients or patients with AIDS) CMV infections may be symptomatic and may result in significant maternal morbidity and mortality. The transmission of CMV to the fetus is a result of maternal viremia and transplacental infection. Perinatal infection can also occur from exposure of the neonate to CMV shedding in the genital tract. Approximately 10% of children with congenital CMV infection are symptomatic at birth. Mortality in these infants is about 10% and approximately 50 to 90% of symptomatic surviving newborns experience significant morbidity, including mental retardation, sensorineural hearing loss, microcephaly, seizures, and other medical problems. The risk of congenital CMV infection resulting from primary maternal CMV infection may be higher and of greater severity than that resulting from maternal reactivation of CMV infection.
Data
Animal Data
At doses resulting in two-times the human exposure of ganciclovir (all dose comparisons presented are based on the human AUC following a single intravenous infusion of 5 mg per kg of ganciclovir) resulted in maternal and embryofetal toxicity in pregnant mice and rabbits as well as teratogenicity in the rabbits. Fetal resorptions were present in at least 85% of rabbits and mice. Rabbits showed increased embryofetal mortality, growth retardation of the fetuses and structural abnormalities of multiple organs of the fetuses including the palate (cleft palate), eyes (anophthalmia/microphthalmia), brain (hydrocephalus), jaw (brachygnathia), kidneys and pancreas (aplastic organs). Increased embryofetal mortality was also seen in mice. Daily intravenous doses of approximately 1.7-times the human exposure (based on AUC) administered to female mice prior to mating, during gestation, and during lactation caused hypoplasia of the testes and seminal vesicles in the male offspring, as well as pathologic changes in the nonglandular region of the stomach.
Data from an ex-vivo human placental model showed that ganciclovir crosses the human placenta. The transfer occurred by passive diffusion and was not saturable over a concentration range of 1 to 10 mg/mL.

8.2 Lactation

Risk Summary
No data are available regarding the presence of valganciclovir (prodrug) or ganciclovir (active drug) in human milk, the effects on the breastfed infant, or the effects on milk production. The Centers for Disease Control and Prevention recommend that HIV-infected mothers not breastfeed their infants to avoid risking postnatal transmission of HIV. Advise nursing mothers that breastfeeding is not recommended during treatment with valganciclovir tablets because of the potential for serious adverse events in nursing infants and because of the potential for transmission of HIV [see Boxed Warning, Warnings and Precautions (5.1, 5.2,5.3,5.4), Nonclinical Toxicology (13.1)].

8.3 Females and Males of Reproductive Potential

Pregnancy Testing
Females of reproductive potential should undergo pregnancy testing before initiation of valganciclovir tablets [see Use in Specific Populations (8.1)].
Contraception
Females
Because of the mutagenic and teratogenic potential of valganciclovir tablets, females of reproductive potential should be advised to use effective contraception during treatment and for at least 30 days following treatment with valganciclovir tablets [see Dosage and Administration (2.6), Warnings and Precautions (5.3, 5.4), Nonclinical Toxicology (13.1)].
Males
Because of its mutagenic potential, males should be advised to practice barrier contraception during and for at least 90 days following, treatment with valganciclovir tablets [see Dosage and Administration (2.6), Warnings and Precautions (5.3), Nonclinical Toxicology (13.1)].

Infertility
Valganciclovir tablets at the recommended doses may cause temporary or permanent female and male infertility [see Warnings and Precautions (5.2), Nonclinical Toxicology (13.1)].

8.4 Pediatric Use

Valganciclovir tablets are indicated for the prevention of CMV disease in pediatric heart transplant patients 4 month to 16 years of age at risk for developing CMV disease [see Indications and Usage (1.2), Dosage and Administration (2.3)].
Study 1 was a safety and pharmacokinetic study in pediatric solid organ transplant patients (kidney, liver, heart, and kidney/pancreas). Valganciclovir tablets were administered once daily within 10 days of transplantation for a maximum of 100 days post-transplantation.
The use of valganciclovir tablets for the prevention of CMV disease in pediatric heart transplant patients 4 month to 16 years of age is based on two studies (Study 1 described above and Study 3) and was supported by previous demonstration of efficacy in adult patients [see Clinical Pharmacology (12.3), Clinical Studies (14.2)] . Study 3 was a pharmacokinetic and safety study of valganciclovir tablets in pediatric heart transplant patients less than 4 months of age who received a single dose of valganciclovir oral solution on each of two consecutive days. A physiologically based pharmacokinetic (PBPK) model was developed based on the available pharmacokinetic data from pediatric and adult patients to support dosing in heart transplant patients less than 1 month of age. However, due to uncertainty in model
predictions for neonates, valganciclovir tablets is not indicated for prophylaxis in this age group.
The safety and efficacy of valganciclovir tablets have not been established in children for prevention of CMV disease in pediatric liver transplant patients, in kidney transplant patients less than 4 months of age, in heart transplant patients less than 1 month of age, in pediatric AIDS patients with CMV retinitis, and in infants with congenital CMV infection.
A pharmacokinetic and pharmacodynamic evaluation of valganciclovir for oral solution was performed in 24 neonates with congenital CMV infection involving the central nervous system. All patients were treated for 6 weeks with a combination of intravenous ganciclovir 6 mg per kg twice daily or valganciclovir for oral solution at doses ranging from 14 mg per kg to 20 mg per kg twice daily. The pharmacokinetic results showed that in infants greater than 7 days to 3 months of age, a dose of 16 mg per kg twice daily of valganciclovir for oral solution provided ganciclovir systemic exposures (median AUC0 to 12h = 23.6 [range 16.8 to 35.5] mcg∙h/mL; n = 6) comparable to those obtained in infants up to 3 months of age from a 6 mg per kg dose of intravenous ganciclovir twice daily (AUC0 to12h = 25.3 [range 2.4 to 89.7] mcg∙h/mL; n = 18) or to the ganciclovir systemic exposures obtained in adults from a 900 mg dose of valganciclovir tablets twice daily. However, the efficacy and safety of intravenous ganciclovir and of valganciclovir have not been established for the treatment of congenital CMV infection in infants and no similar disease occurs in adults; therefore, efficacy cannot be extrapolated from intravenous ganciclovir use in adults.
Pediatric use information for pediatric kidney transplant patients ages 4 months to 16 years and for pediatric heart transplant patients ages 1 to less than 4 months is approved for Roche Palo Alto LLC' s VALCYTE (valganciclovir hydrochloride) tablets. However, due to Roche Palo Alto LLC' s marketing exclusivity rights, this drug product is not labeled with that pediatric information.

8.5 Geriatric Use

Studies of valganciclovir tablets have not been conducted in adults older than 65 years of age. Clinical studies of valganciclovir tablets did not include sufficient numbers of subjects aged 65 and over to determine whether they respond differently from younger subjects. In general, dose selection for an elderly patient should be cautious, usually starting at the low end of the dosing range, reflecting the greater frequency of decreased hepatic, renal, or cardiac function, and of concomitant disease or other drug therapy. Valganciclovir tablets are known to be substantially excreted by the kidneys, and the risk of toxic reactions to this drug may be greater in patients with impaired renal function. Because elderly patients are more likely to have decreased renal function, care should be taken in dose selection. In addition, renal function should be monitored and dosage adjustments should be made accordingly [see Dosage and Administration (2.5), Warnings and Precautions (5.5), Use in Specific Populations (8.6), Clinical Pharmacology (12.3)].

8.6 Renal Impairment

Dose reduction is recommended when administering valganciclovir tablets to patients with renal impairment [see Dosage and Administration (2.5), Warnings and Precautions (5.5), Clinical Pharmacology (12.3)].
For adult patients on hemodialysis (CrCl less than 10 mL/min) valganciclovir tablets should not be used. Adult hemodialysis patients should use ganciclovir in accordance with the dose-reduction algorithm cited in the Cytovene®-IV complete product information section on DOSAGE AND ADMINISTRATION: Renal Impairment [see Dosage and Administration (2.5) and Clinical Pharmacology (12.3)].

8.7 Hepatic Impairment

The safety and efficacy of valganciclovir tablets have not been studied in patients with hepatic impairment.

10 OVERDOSAGE

Experience With Valganciclovir Tablets: One adult developed fatal bone marrow depression (medullary aplasia) after several days of dosing that was at least 10-fold greater than recommended for the patient’s estimated degree of renal impairment.
An overdose of valganciclovir tablets could also possibly result in increased renal toxicity [see Dosage and Administration (2.5), Use in Specific Populations (8.6)].
Because ganciclovir is dialyzable, dialysis may be useful in reducing serum concentrations in patients who have received an overdose of valganciclovir tablets [see Clinical Pharmacology (12.3)]. Adequate hydration should be maintained. The use of hematopoietic growth factors should be considered [see Clinical Pharmacology (12.3)].
Experience with Intravenous Ganciclovir: Reports of overdoses with intravenous ganciclovir have been received from clinical trials and during postmarketing experience. The majority of patients experienced one or more of the following adverse events:
Hematological toxicity: pancytopenia, bone marrow depression, medullary aplasia, leukopenia, neutropenia, granulocytopenia
Hepatotoxicity: hepatitis, liver function disorder
Renal toxicity: worsening of hematuria in a patient with pre-existing renal impairment, acute renal failure, elevated creatinine
Gastrointestinal toxicity: abdominal pain, diarrhea, vomiting
Neurotoxicity: generalized tremor, convulsion

11 DESCRIPTION

Valganciclovir tablets, USP contains valganciclovir hydrochloride, USP a hydrochloride salt of the L-valyl ester of ganciclovir that exists as a mixture of two diastereomers. Ganciclovir is a synthetic guanine derivative active against CMV.
Valganciclovir tablets, USP are available as a 450 mg tablet for oral administration. Each film coated tablet contains 496.3 mg of valganciclovir hydrochloride, USP (corresponding to 450 mg of valganciclovir), and the inactive ingredients crospovidone, microcrystalline cellulose, povidone and stearic acid. The tablets are coated with Opadry Pink which contains hypromellose, iron oxide red, polyethylene glycol, polysorbate 80 and titanium dioxide.
Valganciclovir hydrochloride, USP is a white to off-white powder, slightly hygroscopic with a molecular formula of C14H22N6O5•HCl and a molecular weight of 390.82. The chemical name for valganciclovir hydrochloride, USP is
L-Valine, 2-[(2-amino-1,6-dihydro-6-oxo-9H-purin-9-yl)methoxy]-3-hydroxypropylester, monohydrochloride. Valganciclovir hydrochloride, USP is a polar hydrophilic compound with a solubility of 70 mg/mL in water at 25°C at a pH of 7 and an n-octanol/water partition coefficient of 0.0095 at pH 7. The pKa for valganciclovir hydrochloride, USP is 7.5.
The chemical structure of valganciclovir hydrochloride, USP is:

All doses in this insert are specified in terms of valganciclovir.

12 CLINICAL PHARMACOLOGY

12.1 Mechanism of Action

Valganciclovir is an antiviral drug [see Microbiology (12.4)].

12.3 Pharmacokinetics

Because the major elimination pathway for ganciclovir is renal, dosage reductions according to creatinine clearance are required for valganciclovir tablets [see Dosage and Administration (2.5)].
Pharmacokinetics in Adults: The pharmacokinetics of valganciclovir and ganciclovir after administration of valganciclovir tablets have been evaluated in HIV- and CMV-seropositive patients, patients with AIDS and CMV retinitis, and in solid organ transplant patients.
The ganciclovir pharmacokinetic parameters following administration of 900 mg valganciclovir tablets and 5 mg per kg intravenous ganciclovir and 1000 mg three times daily oral ganciclovir in HIV-positive/CMV-positive patients are summarized in Table 10.
Table 10 Mean Ganciclovir Pharmacokinetic* Measures in Healthy Volunteers and HIV-positive/CMV-positive Adults at Maintenance Dosage

Formulation | Valganciclovir Tablets | Intravenous Ganciclovir | Ganciclovir Capsules
Dosage | 900 mg once daily with food | 5 mg/kg once daily | 1000 mg three times daily with food
AUC0-24h (mcg ·h/mL) | 29.1 ± 9.7 (3 studies, n=57) | 26.5 ± 5.9 (4 studies, n=68) | Range of means 12.3 to 19.2 (6 studies, n=94)
Cmax (mcg/mL) | 5.61 ± 1.52 (3 studies, n=58) | 9.46 ± 2.02 (4 studies, n=68) | Range of means 0.955 to 1.40 (6 studies, n=94)
Absolute oral bioavailability (%) | 59.4 ± 6.1 (2 studies, n=32) | Not Applicable | Range of means 6.22 ± 1.29 to 8.53 ± 1.53 (2 studies, n=32)
Elimination half-life (hr) | 4.08 ± 0.76 (4 studies, n=73) | 3.81 ± 0.71 (4 studies, n=69) | Range of means 3.86 to 5.03 (4 studies, n=61)
Renal clearance (mL/min/kg) | 3.21 ± 0.75 (1 study, n=20) | 2.99 ± 0.67 (1 study, n=16) | Range of means 2.67 to 3.98 (3 studies, n=30)

*Data were obtained from single and multiple dose studies in healthy volunteers, HIV-positive patients, and HIV-positive/CMV-positive patients with and without retinitis. Patients with CMV retinitis tended to have higher ganciclovir plasma concentrations than patients without CMV retinitis.
The area under the plasma concentration-time curve (AUC) of ganciclovir administered as valganciclovir tablets (900 mg once daily) is comparable to the AUC of ganciclovir after administration of intravenous ganciclovir (5 mg per kg once daily). The Cmax of ganciclovir following valganciclovir tablets administration is 40% lower than the Cmax following intravenous ganciclovir administration. During maintenance dosing, ganciclovir AUC0 to 24h and Cmax following oral ganciclovir administration (1000 mg three times daily) are lower relative to valganciclovir tablets and intravenous ganciclovir. The ganciclovir Cmin following intravenous ganciclovir and valganciclovir tablets administration are less than the ganciclovir Cmin following oral ganciclovir administration. The clinical significance of the differences in ganciclovir pharmacokinetics after administration of valganciclovir tablets, ganciclovir capsules, and intravenous ganciclovir is unknown. Figure 1 Ganciclovir Plasma Concentration Time Profiles in HIV-positive/CMV-positive Patients*

*Plasma concentration-time profiles for ganciclovir (GCV) from valganciclovir (VGCV) and intravenous ganciclovir were obtained from a multiple dose study (n=21 and n=18, respectively) in HIV-positive/CMV-positive patients with CMV retinitis. The plasma concentration-time profile for oral ganciclovir was obtained from a multiple dose study (n=24) in HIV-positive/CMV-positive patients without CMV retinitis.
In solid organ transplant recipients, the mean systemic exposure to ganciclovir was 1.7x higher following administration of 900 mg valganciclovir tablets once daily versus 1000 mg ganciclovir capsules three times daily, when both drugs were administered according to their renal function dosing algorithms. The systemic ganciclovir exposures attained were comparable across kidney, heart and liver transplant recipients based on a population pharmacokinetics evaluation (see Table 11).
Table 11 Mean Ganciclovir Pharmacokinetic Measures by Organ Transplant Type

Parameter | Ganciclovir Capsules | Valganciclovir Tablets
Dosage | 1000 mg three times daily with food Mean ± SD | 900 mg once daily with food Mean ± SD
Heart Transplant Recipients | N=13 | N=17
AUC0-24h (mcg·h/mL) | 26.6 ± 11.6 | 40.2 ± 11.8
Cmax (mcg/mL) | 1.4 ± 0.5 | 4.9 ± 1.1
Elimination half-life (hr) | 8.47 ± 2.84 | 6.58 ± 1.50
Liver Transplant Recipients | N=33 | N=75
AUC0-24h (mcg·h/mL) | 24.9 ± 10.2 | 46 ± 16.1
Cmax (mcg/mL) | 1.3 ± 0.4 | 5.4 ± 1.5
Elimination half-life (hr) | 7.68 ± 2.74 | 6.18 ± 1.42
Kidney Transplant Recipients* | N=36 | N=68
AUC0-24h (mcg·h/mL) | 31.3 ± 10.3 | 48.2 ± 14.6
Cmax (mcg/mL) | 1.5 ± 0.5 | 5.3 ± 1.5
Elimination half-life (hr) | 9.44 ± 4.37 | 6.77 ± 1.25

* Includes kidney-pancreas

The pharmacokinetic parameters of ganciclovir following 200 days of valganciclovir tablets administration in high-risk kidney transplant patients were similar to those previously reported in solid organ transplant patients who received valganciclovir tablets for 100 days.
In a pharmacokinetic study in liver transplant patients, the ganciclovir AUC0 to 24h achieved with 900 mg valganciclovir was 41.7 ± 9.9 mcg•h/mL (n=28) and the AUC0 to 24h achieved with the approved dosage of 5 mg per kg intravenous ganciclovir was 48.2 ± 17.3 mcg•h/mL (n=27).
Absorption: Valganciclovir, a prodrug of ganciclovir, is well absorbed from the gastrointestinal tract and rapidly metabolized in the intestinal wall and liver to ganciclovir. The absolute bioavailability of ganciclovir from valganciclovir tablets following administration with food was approximately 60% (3 studies, n=18; n=16; n=28). Ganciclovir median Tmax following administration of 450 mg to 2625 mg valganciclovir tablets ranged from 1 to 3 hours. Dose proportionality with respect to ganciclovir AUC following administration of valganciclovir tablets was demonstrated only under fed conditions. Systemic exposure to the prodrug, valganciclovir, is transient and low, and the AUC24 and Cmax values are approximately 1% and 3% of those of ganciclovir, respectively.
Food Effects: When valganciclovir tablets were administered with a high fat meal containing approximately 600 total calories (31.1 g fat, 51.6 g carbohydrates and 22.2 g protein) at a dose of 875 mg once daily to 16 HIV-positive subjects, the steady-state ganciclovir AUC increased by 30% (95% CI 12% to 51%), and the Cmax increased by 14% (95% CI -5% to 36%), without any prolongation in time to peak plasma concentrations (Tmax). Valganciclovir tablets should be administered with food [see Dosage and Administration (2.1)].
Distribution: Due to the rapid conversion of valganciclovir to ganciclovir, plasma protein binding of valganciclovir was not determined. Plasma protein binding of ganciclovir is 1% to 2% over concentrations of 0.5 and 51 mcg/mL. When ganciclovir was administered intravenously, the steady-state volume of distribution of ganciclovir was 0.703 ± 0.134 L/kg (n=69).
After administration of valganciclovir tablets, no correlation was observed between ganciclovir AUC and reciprocal weight; oral dosing of valganciclovir tablets according to weight is not required.
Metabolism: Valganciclovir is rapidly hydrolyzed to ganciclovir; no other metabolites have been detected. No metabolite of orally administered radiolabeled ganciclovir (1000 mg single dose) accounted for more than 1% to 2% of the radioactivity recovered in the feces or urine.
Elimination: The major route of elimination of valganciclovir is by renal excretion as ganciclovir through glomerular filtration and active tubular secretion. Systemic clearance of intravenously administered ganciclovir was 3.07 ± 0.64 mL/min/kg (n=68) while renal clearance was 2.99 ± 0.67 mL/min/kg (n=16).
The terminal half-life (t½) of ganciclovir following oral administration of valganciclovir tablets to either healthy or HIV-positive/CMV-positive subjects was 4.08 ± 0.76 hours (n=73), and that following administration of intravenous ganciclovir was 3.81 ± 0.71 hours (n=69). In heart, kidney, kidney-pancreas, and liver transplant patients, the terminal elimination half-life of ganciclovir following oral administration of valganciclovir tablets were 6.48 ± 1.38 hours, and following oral administration of ganciclovir capsules was 8.56 ± 3.62 hours.
Specific Populations:
Renal Impairment: The pharmacokinetics of ganciclovir from a single oral dose of 900 mg valganciclovir tablets were evaluated in 24 otherwise healthy individuals with renal impairment.
Table 12 Pharmacokinetics of Ganciclovir from a Single Oral Dose of 900 mg Valganciclovir Tablets

Estimated Creatinine Clearance (mL/min) | N | Apparent Clearance (mL/min) Mean ± SD | AUClast (mcg·h/mL) Mean ± SD | Half-life (hours) Mean ± SD
51-70 | 6 | 249 ± 99 | 49.5 ± 22.4 | 4.85 ± 1.4
21-50 | 6 | 136 ± 64 | 91.9 ± 43.9 | 10.2 ± 4.4
11-20 | 6 | 45 ± 11 | 223 ± 46 | 21.8 ± 5.2
≤10 | 6 | 12.8 ± 8 | 366 ± 66 | 67.5 ± 34

Decreased renal function results in decreased clearance of ganciclovir from valganciclovir, and a corresponding increase in terminal half-life. Therefore, dosage adjustment is required for patients with impaired renal function.
Hemodialysis reduces plasma concentrations of ganciclovir by about 50% following valganciclovir tablets administration. Adult patients receiving hemodialysis (CrCl less than 10 mL/min) cannot use valganciclovir tablets because the daily dose of valganciclovir tablets required for these patients is less than 450 mg [see Dosage and Administration (2.5) and Use in Specific Populations (8.6)].
Pharmacokinetics in Pediatric Patients: The pharmacokinetics of ganciclovir were evaluated following the administration of valganciclovir in 63 pediatric solid organ transplant patients aged 4 months to 16 years. In these studies, patients received oral doses of valganciclovir (either valganciclovir for oral solution or tablets) to produce exposure equivalent to an adult 900 mg dose [see Dosage and Administration (2.3), Adverse Reactions (6. 1), Use in Specific Populations (8.4), Clinical Studies (14.2)].
The pharmacokinetics of ganciclovir were similar across organ types and age ranges. Based on a population pharmacokinetic evaluation, clearance is influenced by both body weight and renal function, while the central and peripheral volumes of distribution were influenced by weight [see Dosage and Administration (2.5)]. The mean total clearance was 5.3 L/hr (88.3 mL/min) for a patient with creatinine clearance of 70.4 mL/min. The mean ganciclovir Cmax, AUC and half-life by age and organ type in studies using the pediatric valganciclovir dosing algorithm are listed in Table 13. Relative to adult transplant patients (Table 11), AUC values in pediatric patients were somewhat increased, but were within the range considered safe and effective in adults.
Table 13 Ganciclovir Pharmacokinetics by Age in Pediatric Solid Organ Transplant Patientsa

 |  |  | Age Group
Organ | PK Parameter mean (SD) |  | 4 months to ≤ 2 years | > 2 to < 12 years | ≥ 12 years
Heart (N=12) | N |  | 6 | 2 | 4
Heart (N=12) | AUC0-24h (mcg ·h/mL) |  | 55.4 (22.8) | 59.6 (21) | 60.6 (25)
Heart (N=12) | Cmax (mcg/mL) |  | 8.2 (2.5) | 12.5 (1.2) | 9.5 (3.3)
Heart (N=12) | t1/2 (h) |  | 3.8 (1.7) | 2.8 (0.9) | 4.9 (0.8)
Kidney (N=31) | N |  | 2 | 10d,e | 19
Kidney (N=31) | AUC0-24h (mcg ·h/mL) |  | 67.6 (13) | 55.9 (12.1) | 47.8 (12.4)
Kidney (N=31) | Cmax (mcg/mL) |  | 10.4 (0.4) | 8.7 (2.1) | 7.7 (2.1)
Kidney (N=31) | t1/2 (h) |  | 4.5 (1.5) | 4.8 (1) | 6 (1.3)
Liver (N=17) | N |  | 9 | 6 | 2
Liver (N=17) | AUC0-24h (mcg ·h/mL) |  | 69.9 (37) | 59.4 (8.1) | 35.4 (2.8)
Liver (N=17) | Cmax (mcg/mL) |  | 11.9 (3.7) | 9.5 (2.3) | 5.5 (1.1)
Liver (N=17) | t1/2 (h) |  | 2.8 (1.5) | 3.8 (0.7) | 4.4 (0.2)

N= number of patients
a Pharmacokinetic parameters were estimated by using population pharmacokinetic modeling.
dThere was one subject in this age group who received both a kidney and liver transplant. The pharmacokinetic profile for this subject has not been included in this table as it is not possible to determine whether the effects observed are from the kidney/liver transplant or neither.
eThe pharmacokinetic profiles for two subjects in this age group who received kidney transplants have not been included in this table as the data were determined to be non-evaluable.

Pharmacokinetics in Geriatric Patients: The pharmacokinetic characteristics of valganocyclovir tablets in elderly patients have not been established. Because elderly individuals frequently have a reduced glomerular filtration rate, renal function should be assessed before and during administration of valganciclovir tablets [see Dosage and Administration (2.5), Use in Specific Populations (8.5)].
Drug Interactions: In vivo drug-drug interaction studies were not conducted with valganciclovir. However, because valganciclovir is rapidly and extensively converted to ganciclovir, interactions associated with ganciclovir will be expected for valganocyclovir tablets [see Drug Interactions (7)].
Drug-drug interaction studies were conducted in patients with normal renal function. Patients with impaired renal function may have increased concentrations of ganciclovir and the coadministered drug following concomitant administration of valganciclovir tablets and drugs excreted by the same pathway as ganciclovir. Therefore, these patients should be closely monitored for toxicity of ganciclovir and the coadministered drug.
Table 14 and Table 15 provide a listing of established drug interaction studies with ganciclovir. Table 14 provides the effects of coadministered drug on ganciclovir plasma pharmacokinetic parameters, whereas Table 15 provides the effects of ganciclovir on plasma pharmacokinetic parameters of co-administered drug.
Table 14 Results of Drug Interaction Studies with Ganciclovir: Effects of Coadministered Drug on Ganciclovir Pharmacokinetic Parameters

Coadministered Drug | Ganciclovir Dosage | N | Ganciclovir Pharmacokinetic (PK) Parameter
Zidovudine 100 mg every 4 hours | 1000 mg every 8 hours | 12 | AUC ↓ 17 ± 25% (range: -52% to 23%)
Probenecid 500 mg every 6 hours | 1000 mg every8 hours | 10 | AUC ↑ 53 ± 91% (range: -14% to 299%) Ganciclovir renal clearance ↓ 22 ± 20% (range: -54% to -4%)
Mycophenolate Mofetil (MMF) 1.5 g single dose | IV ganciclovir 5 mg/kg single dose | 12 | No effect on ganciclovir PK parameters observed (patients with normal renal function)
Didanosine 200 mg every 12 hours administered 2 hours before ganciclovir | 1000 mg every 8 hours | 12 | AUC ↓ 21 ± 17% (range: -44% to 5%)
Didanosine 200 mg every 12 hours simultaneously administered with ganciclovir | 1000 mg every 8 hours | 12 | No effect on ganciclovir PK parameters observed
Didanosine 200 mg every 12 hours simultaneously administered with ganciclovir | IV ganciclovir 5 mg/kg twice daily | 11 | No effect on ganciclovir PK parameters observed
Didanosine 200 mg every 12 hours simultaneously administered with ganciclovir | IV ganciclovir 5 mg/kg once daily | 11 | No effect on ganciclovir PK parameters observed
Trimethoprim 200 mg once daily | 1000 mg every 8 hours | 12 | Ganciclovir renal clearance ↓ 16.3%Half-life ↑15%

Table 15 Results of Drug Interaction Studies with Ganciclovir: Effects of Ganciclovir on Pharmacokinetic Parameters of Coadministered Drug

Coadministered Drug | Ganciclovir Dosage | N | Coadministered Drug Pharmacokinetic (PK) Parameter
Zidovudine 100 mg every 4 hours | 1000 mg every 8 hours | 12 | AUC0-4 ↑ 19 ± 27% (range: -11% to 74%)
Mycophenolate Mofetil (MMF) 1.5 g single dose | IV ganciclovir 5 mg/kg single dose | 12 | No PK interaction observed (patients with normal renal function)
Didanosine 200 mg every 12 hours when administered 2 hours prior to or concurrent with ganciclovir | 1000 mg every 8 hours | 12 | AUC0-12 ↑111 ± 114% (range: 10% to 493%)
Didanosine 200 mg every 12 hours | IV ganciclovir 5 mg/kg twice daily | 11 | AUC0-12 ↑70 ± 40% (range: 3% to 121%)
Didanosine 200 mg every 12 hours | IV ganciclovir 5 mg/kg twice daily | 11 | Cmax↑49 ± 48% (range: -28% to 125%)
Didanosine 200 mg every 12 hours | IV ganciclovir 5 mg/kg once daily | 11 | AUC0-12 ↑50 ± 26% (range: 22% to 110%)
Didanosine 200 mg every 12 hours | IV ganciclovir 5 mg/kg once daily | 11 | Cmax ↑36 ± 36% (range: -27% to 94%)
Trimethoprim 200 mg once daily | 1000 mg every 8 hours | 12 | Increase (12%) in Cmin

Other potential drug interactions
Since ganciclovir is excreted through the kidney via glomerular filtration and active secretion [see Pharmacokinetics (12.3)], coadministration of valganciclovir with antiretroviral drugs that share the tubular secretion pathway, such as nucleos(t)ide reverse transcriptase inhibitors, may change the plasma concentrations of valganciclovir and/or the coadministered drug.
Pediatric use information for pediatric kidney transplant patients ages 4 months to 16 years and for pediatric heart transplant patients ages 1 to less than 4 months is approved for Roche Palo Alto LLC' s VALCYTE (valganciclovir hydrochloride) tablets. However, due to Roche Palo Alto LLC' s marketing exclusivity rights, this drug product is not labeled with that pediatric information.

12.4 Microbiology

Mechanism of Action: Valganciclovir is an L-valyl ester (prodrug) of ganciclovir that exists as a mixture of two diastereomers. After oral administration, both diastereomers are rapidly converted to ganciclovir by intestinal and hepatic esterases. Ganciclovir is a synthetic analogue of 2'-deoxyguanosine, which inhibits replication of human CMV in cell culture and in vivo.
In CMV-infected cells ganciclovir is initially phosphorylated to ganciclovir monophosphate by the viral protein kinase, pUL97. Further phosphorylation occurs by cellular kinases to produce ganciclovir triphosphate, which is then slowly metabolized intracellularly (half-life 18 hours). As the phosphorylation is largely dependent on the viral kinase, phosphorylation of ganciclovir occurs preferentially in virus-infected cells. The virustatic activity of ganciclovir is due to inhibition of the viral DNA polymerase, pUL54, synthesis by ganciclovir triphosphate.
Antiviral Activity: The quantitative relationship between the cell culture susceptibility of human herpes viruses to antivirals and clinical response to antiviral therapy has not been established, and virus sensitivity testing has not been standardized. Sensitivity test results, expressed as the concentration of drug required to inhibit the growth of virus in cell culture by 50% (EC50), vary greatly depending upon a number of factors including the assay used. Thus, the reported EC50 values of ganciclovir that inhibit human CMV replication in cell culture (laboratory and clinical isolates) have ranged from 0.08 to 22.94 μM (0.02 to 5.75 mcg/mL). The distribution and range in susceptibility observed in one assay evaluating 130 clinical isolates was 0 to 1 μM (35%), 1.1 to 2 μM (20%), 2.1 to 3 μM (27%), 3.1 to 4 μM (13%), 4.1 to 5 μM (5%), less than 5 μM (less than 1%). Ganciclovir inhibits mammalian cell proliferation (CC50) in cell culture at higher concentrations ranging from 40 to > 1,000 μM (10.21 to > 250 mcg/mL). Bone marrow-derived colony-forming cells are more sensitive [CC50 value = 2.7 to 12 μM (0.69 to 3.06 mcg/mL)].
Viral Resistance:
Cell culture: CMV isolates with reduced susceptibility to ganciclovir have been selected in cell culture. Growth of CMV strains in the presence of ganciclovir resulted in the selection of amino acid substitutions in the viral protein kinase pUL97 (M460I/V, L595S, G598D, and K599T) and the viral DNA polymerase pUL54 (D301N, N410K, F412V, P488R, L516R, C539R, L545S, F595I, V812L, P829S, L862F, D879G, and V946L).
In vivo: Viruses resistant to ganciclovir can arise after prolonged treatment or prophylaxis with valganciclovir by selection of substitutions in pUL97 and/or pUL54. Limited clinical data are available on the development of clinical resistance to ganciclovir and many pathways to resistance likely exist. In clinical isolates, seven canonical pUL97 substitutions, (M460V/I, H520Q, C592G, A594V, L595S, C603W) are the most frequently reported ganciclovir resistance-associated substitutions. These and other substitutions less frequently reported in the literature, or observed in clinical trials, are listed in Table 16.
Table 16 Summary of Resistance-associated Amino Acid Substitutions Observed in the CMV of Patients Failing Ganciclovir Treatment or Prophylaxis

pUL97 | L405P, A440V, M460I/V/T, V466G/M, C518Y, H520Q, del 590-593, A591D/V, C592G, A594E/G/T/V/P, L595F/S/T/W, del 595, del 595-603, E596D/G, K599E/M, del 600-601, del 597-600, del 601-603, C603W/R/S/Y, C607F/S/Y, A613V
pUL54 | E315D, N408D/K/S, F412C/L/S, D413A/E, L501F/I, T503I, K513E/N/R, I521T, P522A/L/S, L545S/W, Q578H/L, D588E/N, G629S, S695T, I726T/V, E756K, V781I, V787L, L802M, A809V, T813S, T821I, A834P, G841A/S, D879G, A972V, del 981-982, A987G

Note: Many additional pathways to ganciclovir resistance likely exist

The presence of known ganciclovir resistance-associated amino acid substitutions was evaluated in a study that extended valganciclovir CMV prophylaxis from 100 days to 200 days post-transplant in adult kidney transplant patients at high risk for CMV disease (D+/R-) [see Clinical Studies (14.1)]. Five subjects from the 100 day group and four subjects from the 200 day group meeting the resistance analysis criteria had known ganciclovir resistance-associated amino acid substitutions detected. In six subjects, the following resistance-associated amino acid substitutions were detected within pUL97: 100 day group: A440V, M460V, C592G; 200 day group: M460V, C603W. In three subjects, the following resistance-associated amino acid substitutions were detected within pUL54: 100 day group: E315D, 200 day group: E315D, P522S. Overall, the detection of known ganciclovir resistance-associated amino acid substitutions was observed more frequently in patients during prophylaxis therapy than after the completion of prophylaxis therapy (during therapy: 5/12 [42%] versus after therapy: 4/58 [7%]). The possibility of viral resistance should be considered in patients who show poor clinical response or experience persistent viral excretion during therapy.
Cross-Resistance: Cross-resistance has been reported for amino acid substitutions selected in cell culture by ganciclovir, cidofovir or foscarnet. In general, amino acid substitutions in pUL54 conferring cross-resistance to ganciclovir and cidofovir are located within the exonuclease domains and region V. Whereas, amino acid substitutions conferring cross-resistance to foscarnet are diverse, but concentrate at and between regions II (codon 696-742) and III (codon 805-845). The amino acid substitutions that resulted in reduced susceptibility to ganciclovir and either cidofovir and/or foscarnet are summarized in Table 17.
Substitutions at amino acid positions pUL97 340 to 400 have been found to confer resistance to ganciclovir. Resistance data based on assays that do not include this region should be interpreted cautiously.
Table 17 Summary of pUL54 Amino Acid Substitutions with Cross-Resistance between Ganciclovir, Cidofovir, and/or Foscarnet

Cross-resistant to cidofovir | D301N, N408D/K, N410K, F412C/L/S/V, D413E, L501I, T503I, K513E/N, L516R, I521T, P522S/A, L545S/W, Q578H, D588N, I726T/V, E756K, V812L, T813S, A834P, G841A, del 981-982, A987G
Cross-resistant to foscarnet | F412C, Q578H/L, D588N, E756K, V781I, V787L, L802M, A809V, V812L, T813S, T821I, A834P, G841A, del 981-982

13 NONCLINICAL TOXICOLOGY

13.1 Carcinogenesis & Mutagenesis & Impairment Of Fertility

Long-term carcinogenicity studies have not been conducted with valganciclovir tablets. However, upon oral administration, valganciclovir is rapidly and extensively converted to ganciclovir. Therefore, like ganciclovir, valganciclovir is a potential carcinogen.
Ganciclovir was carcinogenic in the mouse at oral doses that produced exposures approximately 0.1x and 1.4x, respectively, the mean drug exposure in humans following the recommended intravenous dose of 5 mg/kg, based on area under the plasma concentration curve (AUC) comparisons. At the higher dose there was a significant increase in the incidence of tumors of the preputial gland in males, forestomach (nonglandular mucosa) in males and females, and reproductive tissues (ovaries, uterus, mammary gland, clitoral gland and vagina) and liver in females. At the lower dose, a slightly increased incidence of tumors was noted in the preputial and harderian glands in males, forestomach in males and females, and liver in females. Ganciclovir should be considered a potential carcinogen in humans.
Valganciclovir increases mutations in mouse lymphoma cells. In the mouse micronucleus assay, valganciclovir was clastogenic. Valganciclovir was not mutagenic in the Ames Salmonella assay. Ganciclovir increased mutations in mouse lymphoma cells and DNA damage in human lymphocytes in vitro. In the mouse micronucleus assay, ganciclovir was clastogenic. Ganciclovir was not mutagenic in the Ames Salmonella assay.
Valganciclovir is converted to ganciclovir and therefore is expected to have similar reproductive toxicity effects as ganciclovir [see Warnings and Precautions (5.2)]. Ganciclovir caused decreased mating behavior, decreased fertility, and an increased incidence of embryolethality in female mice following intravenous doses that produced an exposure approximately 1.7x the mean drug exposure in humans following the dose of 5 mg per kg, based on AUC comparisons. Ganciclovir caused decreased fertility in male mice and hypospermatogenesis in mice and dogs following daily oral or intravenous administration. Systemic drug exposure (AUC) at the lowest dose showing toxicity in each species ranged from 0.03 to 0.1x the AUC of the recommended human intravenous dose. Valganciclovir caused similar effects on spermatogenesis in mice, rats, and dogs. These effects were reversible at lower doses but irreversible at higher doses. It is considered likely that ganciclovir (and valganciclovir) could cause temporary or permanent inhibition of human spermatogenesis.

14 CLINICAL STUDIES

14.1 Adult Patients

Induction Therapy of CMV Retinitis: In one randomized open-label controlled study, 160 patients with AIDS and newly diagnosed CMV retinitis were randomized to receive treatment with either valganciclovir tablets (900 mg twice daily for 21 days, then 900 mg once daily for 7 days) or with intravenous ganciclovir solution (5 mg per kg twice daily for 21 days, then 5 mg per kg once daily for 7 days). Study participants were: male (91%), White (53%), Hispanic (31%), and Black (11%). The median age was 39 years, the median baseline HIV-1 RNA was 4.9 log10, and the median CD4 cell count was 23 cells/mm3. A determination of CMV retinitis progression by the masked review of retinal photographs taken at baseline and Week 4 was the primary outcome measurement of the 3-week induction therapy. Table 18 provides the outcomes at 4 weeks.
Table 18 Week 4 Masked Review of Retinal Photographs in CMV Retinitis Study

 | Intravenous Ganciclovir | Valganciclovir Tablets
Determination of CMV retinitis progression at Week 4 | N=80 | N=80
Progressor Non-progressor | 7 63 | 7 64
Death Discontinuations due to Adverse Events Failed to return | 2 1 1 | 1 2 1
CMV not confirmed at baseline or no interpretable baseline photos | 6 | 5

Maintenance Therapy of CMV Retinitis: No comparative clinical data are available on the efficacy of valganciclovir tablets for the maintenance therapy of CMV retinitis because all patients in the CMV retinitis study received open-label valganciclovir tablets after Week 4. However, the AUC for ganciclovir is similar following administration of 900 mg valganciclovir tablets once daily and 5 mg per kg intravenous ganciclovir once daily. Although the ganciclovir Cmax is lower following valganciclovir tablets administration compared to intravenous ganciclovir, it is higher than the Cmax obtained following oral ganciclovir administration [see Figure 1 in Clinical Pharmacology (12.3)]. Therefore, use of valganciclovir tablets as maintenance therapy is supported by a plasma concentration-time profile similar to that of two approved products for maintenance therapy of CMV retinitis.
Prevention of CMV Disease in Heart, Kidney, Kidney-Pancreas, or Liver Transplantation: A double blind, double-dummy active comparator study was conducted in 372 heart, liver, kidney, or kidney-pancreas transplant patients at high risk for CMV disease (D+/R-). Patients were randomized (2 valganciclovir tablets: 1 oral ganciclovir) to receive either valganciclovir tablets (900 mg once daily) or oral ganciclovir (1000 mg three times a day) starting within 10 days of transplantation until Day 100 post-transplant. The proportion of patients who developed CMV disease, including CMV syndrome and/or tissue-invasive disease during the first 6 months post-transplant was similar between the valganciclovir tablets arm (12.1%, N=239) and the oral ganciclovir arm (15.2%, N=125). However, in liver transplant patients, the incidence of tissue-invasive CMV disease was significantly higher in the valganciclovir group compared with the ganciclovir group. These results are summarized in Table 19.
Mortality at six months was 3.7% (9/244) in the valganciclovir tablets group and 1.6% (2/126) in the oral ganciclovir group.
Table 19 Percentage of Patients with CMV Disease, Tissue-Invasive CMV Disease or CMV syndrome by Organ Type: Endpoint Committee, 6 Month ITT Population

 | CMV Disease^1 |  | Tissue-Invasive CMV Disease |  | CMV Syndrome^2
Organ | VGCV(N=239) | GCV(N=125) | VGCV (N=239) | GCV (N=125) | VGCV (N=239) | GCV (N=125)
Liver | 19 % | 12 % | 14 % | 3 % | 5 % | 9 %
(n=177) | (22 / 118) | (7 / 59) | (16 / 118) | (2 / 59) | (6 / 118) | (5 / 59)
Kidney | 6 % | 23 % | 1 % | 5 % | 5 % | 18 %
(n=120) | (5 / 81) | (9 / 39) | (1 / 81) | (2 / 39) | (4 / 81) | (7 / 39)
Heart | 6 % | 10 % | 0 % | 5 % | 6 % | 5 %
(n=56) | (2 / 35) | (2 / 21) | (0 / 35) | (1 / 21) | (2 / 35) | (1 / 21)
Kidney / Pancreas | 0 % | 17 % | 0 % | 17 % | 0% | 0 %
(n=11) | (0 / 5) | (1 / 6) | (0 / 5) | (1 / 6) | (0 / 5) | (0 / 6)

GCV = oral ganciclovir; VGCV = valganciclovir
^1Number of patients with CMV disease = Number of patients with tissue-invasive CMV disease or CMV syndrome
^2CMV syndrome was defined as evidence of CMV viremia accompanied with fever greater than or equal to 38°C on two or more occasions separated by at least 24 hours within a 7-day period and one or more of the following: malaise, leukopenia, atypical lymphocytosis, thrombocytopenia, and elevation of hepatic transaminases
Prevention of CMV Disease in Kidney Transplantation: A double-blind, placebo-controlled study was conducted in 326 kidney transplant patients at high risk for CMV disease (D+/R-) to assess the efficacy and safety of extending valganciclovir tablets CMV prophylaxis from 100 to 200 days post-transplant. Patients were randomized (1:1) to receive valganciclovir tablets (900 mg once daily) within 10 days of transplantation either until Day 200 post-transplant or until Day 100 post-transplant followed by 100 days of placebo. Extending CMV prophylaxis with valganciclovir tablets until Day 200 post-transplant demonstrated superiority in preventing CMV disease within the first 12 months post-transplant in high risk kidney transplant patients compared to the 100 day dosing regimen (primary endpoint). These results are summarized in Table 20.
Table 20 Percentage of Kidney Transplant Patients with CMV Disease, Tissue-Invasive CMV Disease or CMV Syndrome, 12 Month ITT Population

 | CMV Disease^1 |  | Tissue-Invasive CMV Disease |  | CMV Syndrome^2
 | 100 Days VGCV (N=163) | 200 Days VGCV (N=155) | 100 Days VGCV (N=163) | 200 Days VGCV (N=155) | 100 Days VGCV (N=163) | 200 Days VGCV (N=155)
Cases | 36.8% (60/163) | 16.8% (26/155) | 1.8% (3/163)^3 | 0.6% (1/155) | 35% (57/163) | 16.1% (25/155)

VGCV = valganciclovir.
^1Number of patients with CMV disease = Number of patients with tissue-invasive CMV disease or CMV syndrome
^2CMV syndrome was defined as evidence of CMV viremia accompanied with at least one of the followings: fever (greater than or equal to 38°C), severe malaise, leukopenia, atypical lymphocytosis, thrombocytopenia, and elevation of hepatic transaminases
^3Two patients in the 100 day group had both tissue-invasive CMV disease and CMV syndrome; however, these patients are counted as having only tissue-invasive CMV disease.
The percentage of kidney transplant patients with CMV disease at 24 months post-transplant was 38.7% (63/163) for the 100 day dosing regimen and 21.3% (33/155) for the 200 day dosing regimen.

14.2 Pediatric Patients

Prevention of CMV in Pediatric Heart, Kidney, or Liver Transplantation: Sixty-three children, 4 months to 16 years of age, who had a solid organ transplant (kidney 33, liver 17, heart 12, and kidney/liver 1) and were at risk for developing CMV disease, were enrolled in an open-label, safety, and pharmacokinetic study of oral valganciclovir (valganciclovir for oral solution or tablets). Patients received valganciclovir tablets once daily within 10 days after transplant until a maximum of 100 days post-transplant. The daily doses of valganciclovir tablets were calculated at each study visit based on body surface area and a modified creatinine clearance [see Dosage and Administration (2.3)].
The pharmacokinetics of ganciclovir were similar across organ transplant types and age ranges. The mean daily ganciclovir exposures in pediatric patients were somewhat increased relative to those observed in adult solid organ transplant patients receiving valganciclovir tablets 900 mg once daily, but were within the range considered safe and effective in adults [see Clinical Pharmacology (12.3)]. No case of CMV syndrome or tissue-invasive CMV disease was reported within the first six months post-transplantation.
Pediatric use information for pediatric kidney transplant patients ages 4 months to 16 years and for pediatric heart transplant patients ages 1 to less than 4 months is approved for Roche Palo Alto LLC' s VALCYTE (valganciclovir hydrochloride) tablets. However, due to Roche Palo Alto LLC' s marketing exclusivity rights, this drug product is not labeled with that pediatric information.

15 REFERENCES

noninvasive assessment of body composition and growth. J of Ped 1986: 109(4): 698707.

Safety and Health, DHHS (NIOSH) Publication No. 2014138 (Supersedes 2012150).

16 HOW SUPPLIED/STORAGE AND HANDLING

contains 496.3 mg of valganciclovir hydrochloride, USP equivalent to 450 mg of valganciclovir. Valganciclovir tablets are supplied as:
NDC 50268-787-12 5 tablets per card, 4 cards per carton.
Store at 25oC; excursions permitted between 15o and 30oC (59o and 86oF). [See USP Controlled Room Temperature.]
Dispensed in Unit Dose Material. For Institutional Use Only.

17 PATIENT COUNSELING INFORMATION

Advise the patient to read the FDA-approved patient labeling (Patient Information and Instructions for Use).
Serious Adverse Reactions
Inform patients that valganciclovir tablets may cause granulocytopenia (neutropenia), anemia, thrombocytopenia and elevated creatinine levels and that dose modification or discontinuation of dosing may be required. Complete blood counts, platelet counts, and creatinine levels should be performed frequently during treatment [see Warnings and Precautions (5.1)].

Pregnancy and Contraception
Inform females of reproductive potential that valganciclovir tablets causes birth defects in animals. Advise them to use effective contraception during and for at least 30 days following treatment with valganciclovir tablets. Similarly, advise males to practice barrier contraception during and for at least 90 days following treatment with valganciclovir tablets [see Use in Specific Populations (8.1, 8.3)].
Carcinogenicity
Advise patients that valganciclovir is considered a potential carcinogen [see Nonclinical Toxicity (13.1)].
Lactation
Advise mothers not to breast-feed if they are receiving valganciclovir tablets because of the potential for hematologic toxicity and cancer in nursing infants, and because HIV can be passed to the baby in breast milk [see Use in Specific Populations (8.2)].
Infertility
Advise patients that valganciclovir tablets may cause temporary or permanent female and male infertility [see Warnings and Precautions (5.2), Use in Specific Populations (8.3)].
Impairment of Cognitive Ability
Inform patients that tasks requiring alertness may be affected including the patient’s ability to drive and operate machinery as convulsions, sedation, dizziness, ataxia and/or confusion have been reported with the use of valganciclovir tablets [see Adverse Reactions (6.1)].
Use in Patients with CMV Retinitis
Inform patients that valganciclovir is not a cure for CMV retinitis, and they may continue to experience progression of retinitis during or following treatment. Advise patients to have ophthalmologic follow-up examinations at a minimum of every 4 to 6 weeks while being treated with valganciclovir tablets. Some patients will require more frequent follow-up.
Administration
Inform adult patients that they should use valganciclovir tablets, not valganciclovir for oral solution [see Dosage and Administration (2.1)].
Inform patients to take valganciclovir tablets with food to maximize bioavailability.

Manufactured for:
AvKARE
Pulaski, TN 38478

Mfg. Rev. 03/16
AV Rev. 02/24 (M)
AvPAK

PATIENT INFORMATION

Valganciclovir

(val gan SYE kloe veer)
tablets
What is the most important information I should know about valganciclovir tablets?
• Valganciclovir tablets can affect your blood cells and bone marrow causing serious and life-threatening problems. Valganciclovir tablets can lower the amount of your white blood cells, red blood cells, and platelets. Your healthcare provider may do regular blood tests to check your blood cell counts while you are taking valganciclovir tablets. Based on these tests, your healthcare provider may change your dose or tell you to stop taking valganciclovir tablets.
• Valganciclovir tablets may cause cancer. Valganciclovir tablets causes cancer in animals. It is not known if valganciclovir tablets cause cancer in people.
• Valganciclovir tablets may cause birth defects. Valganciclovir tablets causes birth defects in animals. It is not known if valganciclovir tablets cause birth defects in people. If you are pregnant, talk to your healthcare provider before taking valganciclovir tablets.
• If you are a female who can become pregnant, you should have a pregnancy test done before starting valganciclovir tablets.
• If you are a female who can become pregnant, you should use effective birth control during treatment with valganciclovir tablets and for at least 30 days after treatment.
• Tell your healthcare provider right away if you become pregnant while taking valganciclovir tablets.
• Men should use a condom during treatment with valganciclovir tablets, and for at least 90 days after treatment, if their female sexual partner can become pregnant. Talk to your healthcare provider if you have questions about birth control.
• Valganciclovir tablets may lower the amount of sperm in a man’s body and cause fertility problems. Valganciclovir tablets may also cause fertility problems in women. Talk to your healthcare provider if this is a concern for you.
• Valganciclovir tablets can affect your kidneys, including serious problems such as kidney failure. Your healthcare provider may do regular blood tests to check your kidney function while you are taking valganciclovir tablets. Your healthcare provider may adjust your dose based on these tests.
• Valganciclovir tablets changes into the medicine ganciclovir once it is in your body. Ganciclovir is also the active ingredient in Cytovene®-IV. Do not take Cytovene-IV if you are taking valganciclovir tablets. You could overdose and become very sick if valganciclovir tablets are taken with Cytovene-IV. Talk to your healthcare provider or pharmacist if you have questions about your medicine.

What are valganciclovir tablets?
Valganciclovir tablet is a prescription antiviral medicine.
In adults, valganciclovir tablets are used:
• to treat cytomegalovirus (CMV) retinitis in people who have acquired immunodeficiency syndrome (AIDS). When CMV virus infects the eyes, it is called CMV retinitis. If CMV retinitis is left untreated, it can cause blindness.
• to prevent cytomegalovirus (CMV) disease in people who have received a heart, kidney, or kidney-pancreas transplant and who have a high risk for getting CMV disease.
In children, valganciclovir tablets are used:
• to prevent cytomegalovirus (CMV) disease in children 4 month to 16 years of age who have received a heart transplant and have a high risk for getting CMV disease.
Pediatric use information for pediatric kidney transplant patients ages 4 months to 16 years and for pediatric heart transplant patients ages 1 to less than 4 months is approved for Roche Palo Alto LLC' s VALCYTE (valganciclovir hydrochloride) tablets. However, due to Roche Palo Alto LLC' s marketing exclusivity rights, this drug product is not labeled with that pediatric information.
Valganciclovir tablets do not cure CMV retinitis. You may still get retinitis or worsening of retinitis during or after treatment with valganciclovir tablets. It is important to stay under a healthcare provider’s care and have your eyes checked every 4 to 6 weeks during treatment with valganciclovir tablets.

Who should not take valganciclovir tablets?
Do not take valganciclovir tablets if you are allergic to any of its ingredients or if you have ever had a serious allergic reaction to ganciclovir capsules or Cytovene-IV. Symptoms of an allergic reaction to valganciclovir tablets may include: sudden trouble breathing, wheezing, hives all over your body, swelling around your mouth, or feeling anxious.
See the end of this leaflet for a list of the ingredients in valganciclovir tablets.
What should I tell my healthcare provider before taking valganciclovir tablets?
Before taking valganciclovir tablets, tell your healthcare provider if you:
• have kidney problems. Your healthcare provider may give you a lower dose of valganciclovir tablets, or check you more often if you are taking valganciclovir tablets.
• are receiving hemodialysis.
• have blood cell problems.
• are having radiation treatment.
• have any other medical conditions.
• are pregnant or plan to become pregnant. It is not known if valganciclovir tablets cause birth defects in an unborn baby.
• Tell your healthcare provider right away if you become pregnant while taking valganciclovir tablets. See "What is the most important information I should know about valganciclovir tablets?”

• are breastfeeding or plan to breastfeed. It is not known if valganciclovir passes into your breast milk. You should not breastfeed if you take valganciclovir tablets.
o You should not breastfeed if you have Human Immunodeficiency Virus (HIV-1) because of the risk of passing HIV-1 to your baby.
o Talk to your healthcare provider about the best way to feed your baby.
Tell your healthcare provider about all the medicines you take, including prescription and over-the-counter medicines, vitamins and herbal supplements.
Valganciclovir tablets and other medicines may affect each other and cause serious side effects. Keep a list of your medicines to show your healthcare provider and pharmacist.
• You can ask your healthcare provider or pharmacist for a list of medicines that interact with valganciclovir tablets.
• Do not start taking a new medicine without telling your healthcare provider. Your healthcare provider can tell you if it is safe to take valganciclovir tablets with other medicines.
How should I take valganciclovir tablets?
• Take valganciclovir tablets exactly as your healthcare provider tells you. Your dose of valganciclovir tablets will depend on your medical condition.
• Adults should only take valganciclovir tablets. Children may take either valganciclovir tablets or oral solution.
• Take valganciclovir tablets with food.
• Do not break or crush valganciclovir tablets. Avoid contact with your skin or eyes. If you come in contact with the contents of the tablet or oral solution, wash your skin well with soap and water or rinse your eyes well with plain water.
• If you miss a dose of valganciclovir tablets, take the missed dose as soon as you remember. Then, take the next dose at the usual scheduled time. However, if it is almost time for your next dose, do not take the missed dose.
• Do not let your valganciclovir tablets run out. The amount of virus in your blood may increase if your medicine is stopped, even for a short time.
• If you take too much valganciclovir tablets, call your healthcare provider or go to the nearest hospital emergency room right away.
Talk to your healthcare provider, nurse or pharmacist if you have questions about your medicine.
What should I avoid while taking valganciclovir tablets?
• Valganciclovir tablets can cause seizures, sleepiness, dizziness, unsteady movements, and confusion. You should not drive a car or operate other dangerous machinery until you know how valganciclovir tablets affects you.
What are the possible side effects of valganciclovir tablets?
Valganciclovir tablets may cause serious side effects, including:
See "What is the most important information I should know about valganciclovir tablets?”
Common side effects of valganciclovir tablets in adults and children include:
• diarrhea
• nausea, vomiting • low white cell, red cell and platelet cell counts in blood tests
• fever • rejection of the transplanted organ (graft)
• shaky movements (tremors)

Other common side effects in children include:
• headache • upper respiratory tract infection
• high blood pressure • urinary tract infection
Tell your healthcare provider if you have any side effect that bothers you or that does not go away.
These are not all the possible side effects of valganciclovir tablets. For more information, ask your healthcare provider or pharmacist.
Call your healthcare provider for medical advice about side effects. You may report side effects to FDA at 1-800-FDA-1088.
How should I store valganciclovir tablets?
• Store valganciclovir tablets at 25°C; excursions permitted between 15o and 30oC (59o and 86oF). [See USP Controlled Room Temperature.]
• Do not keep valganciclovir tablets that is out of date or that you no longer need.
• Keep valganciclovir tablets and all medicines out of the reach of children.
General information about the safe and effective use of valganciclovir tablets
Medicines are sometimes prescribed for purposes other than those listed in Patient Information leaflet. Do not use valganciclovir tablets for a condition for which it was not prescribed. Do not give valganciclovir tablets to other people, even if they have the same symptoms you have. It may harm them.
This leaflet summarizes the most important information about valganciclovir tablets. If you would like more information, talk with your healthcare provider. You can ask your healthcare provider or pharmacist for information about valganciclovir tablets that is written for health professionals.
What are the ingredients in valganciclovir tablets?
Active Ingredient: valganciclovir hydrochloride, USP
Inactive Ingredients: crospovidone, microcrystalline cellulose, povidone and stearic acid. The tablets are coated with Opadry Pink which contains hypromellose, iron oxide red, polyethylene glycol, polysorbate 80 and titanium dioxide.
This Patient Information has been approved by the U.S. Food and Drug Administration.

Manufactured for:
AvKARE
Pulaski, TN 38478

Mfg. Rev. 03/16
AV Rev. 02/24 (M)
AvPAK